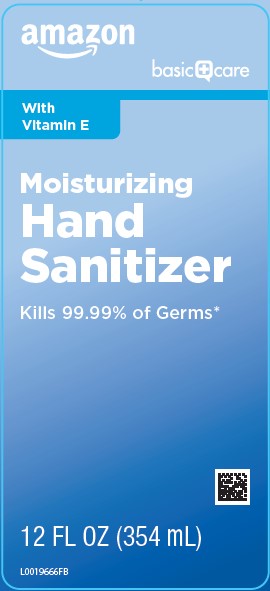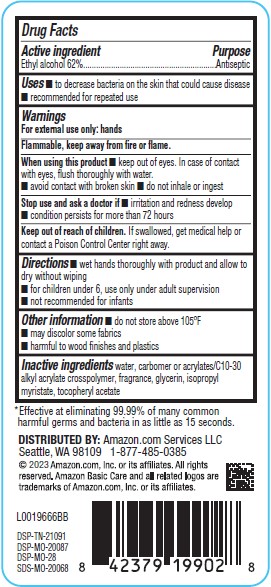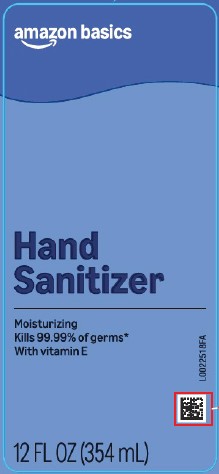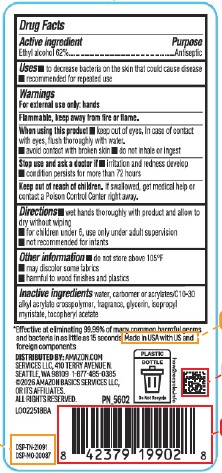 DRUG LABEL: Alcohol
NDC: 72288-849 | Form: LIQUID
Manufacturer: Amazon.com Services LLC
Category: otc | Type: HUMAN OTC DRUG LABEL
Date: 20260216

ACTIVE INGREDIENTS: ALCOHOL 62 mL/100 mL
INACTIVE INGREDIENTS: WATER; CARBOMER HOMOPOLYMER, UNSPECIFIED TYPE; ACRYLATES/C10-30 ALKYL ACRYLATE CROSSPOLYMER (60000 MPA.S); GLYCERIN; ISOPROPYL MYRISTATE; TOCOPHEROL

Basic Care_Basics 849.001/849AA-BA
Moisturizing Hand Sanitizer

Active ingredient

Ethyl Alcohol 62%

Purpose

Antiseptic

Uses

- to decrease bacteria on the skin that could cause disease
- recommended for repeated use

Warnings

For exterenal use only: hands

Flammable, keep away from fire or flame.

When using this product

- keep out of eyes. In case of contact with eyes, flush thoroughly with water.
- avoid contact with broken skin
- do not inhale or ingest

Stop use and ask a doctor if

- irritation and redness develop
- condition persists for more than 72 hours

Keep out of reach of children.

If swallowed, get medical help or contact a Poison Control Center right away.

Directions

- wet hands thoroughly with product and allow to dry without wiping
- for children under 6, use only under adult supervision
- not recommended for infants

Other information

- do not store above 105⁰F
- may discolor some fabrics
- harmful to wood finishes and plastics

Inactive ingredients

water, carbomer or acrylates/C10-30 alkyl acrylate crosspolymer, fragrance, glycerin, isopropyl myristate, tocopheryl acetate

Claims

*Effective at eliminating 99.99% of many common harmful germs and bacteria in as little as 15 seconds.

Made in USA with US and foreign components.

Adverse reaction

DISTRIBUTED BY: Amazon.com Services LLC, 410 Terry Avenue N., Seattle, WA 98109 1-877-485-0385

©2026 Amazon Basic Services LLC, or its affiliates. All rights reserved.

DSP-TN-21091

DSP-MO-20087

PLASTIC BOTTLE

Do Not Recycle

how2recycle.info

Principal display panel

amazon basics

Hand Sanitizer

Moisturizing

Kills 99.99% of germs*

With vitamin E

12 FL OZ (354 mL)

Principal display panel

amazon

basic care

With Vitamin E

Moitsturizing

Hand

Sanitizer

kills 99.99% of Germs*

12 FL OZ (354 mL)